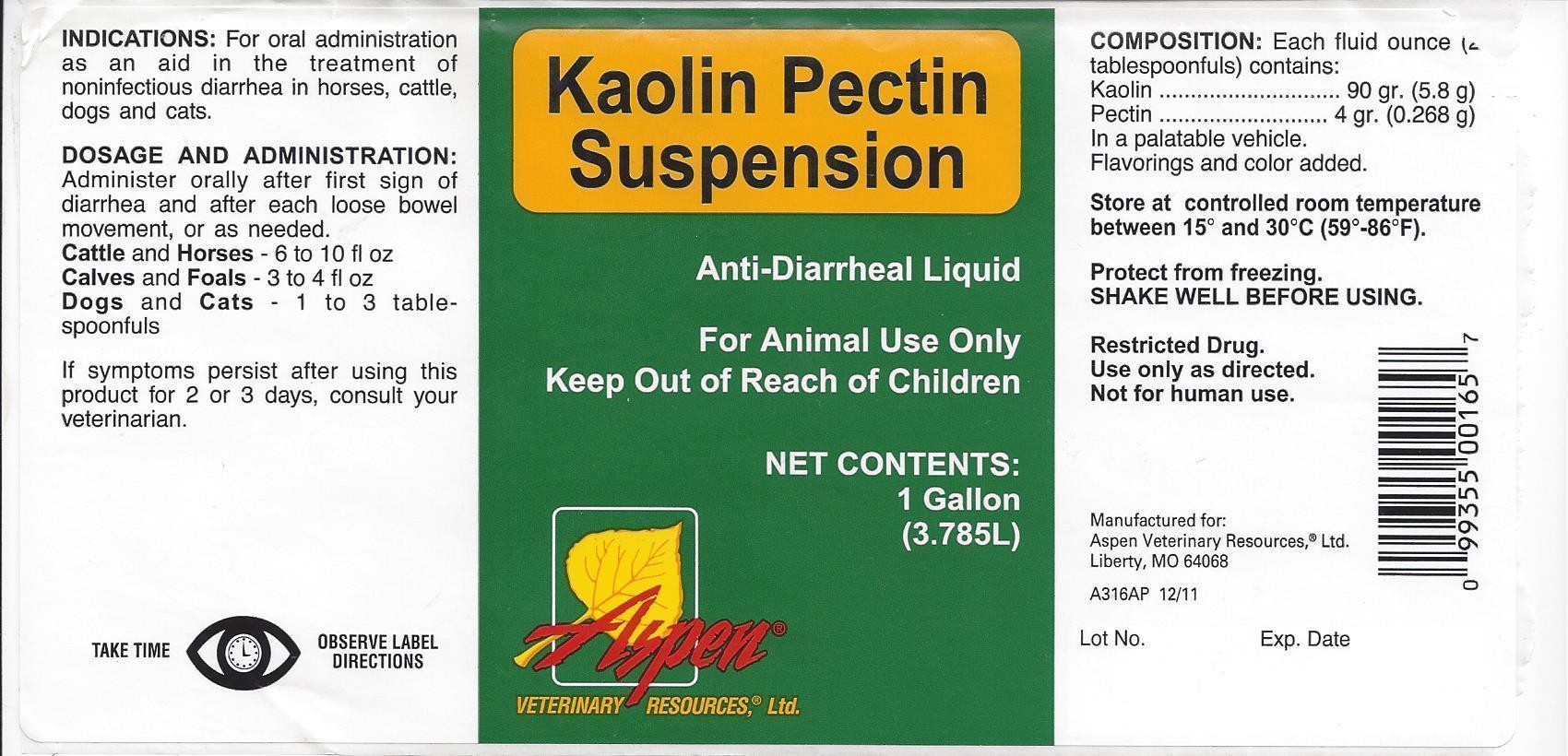 DRUG LABEL: Kaolin Pectin Suspension
NDC: 46066-001 | Form: SUSPENSION
Manufacturer: Aspen Veterinary
Category: animal | Type: OTC ANIMAL DRUG LABEL
Date: 20130916

ACTIVE INGREDIENTS: KAOLIN 196 mg/1 mL; PECTIN, CITRUS 9 mg/1 mL
INACTIVE INGREDIENTS: GUAR GUM; METHYLPARABEN; POTASSIUM SORBATE; SACCHARIN SODIUM; PROPYLPARABEN; FD&C RED NO. 40; WATER

Kaolin Pectin Suspension

Kaolin Pectin Suspension

Anti-Diarrheal Liquid

For Animal Use Only

Keep Out of Reach of Children

NET CONTENTS:

1 GALLON (3.785L)

ASPEN

VETERINARY RESOURCES, Ltd.

INDICATIONS:

For oral administration as an aid in the treatment of noninfectious diarrhea in horses, cattle, dogs and cats.

DOSAGE AND ADMINISTRATION:

Administer orally after first sign of diarrhea and after each loose bowel movement, or as needed.

Cattle and Horses: 6 to 10 fl oz

Calves and Foals: 3 to 4 fl oz

Dogs and Cats: 1 to 3 tablespoonfuls

If symptoms persist after using this product for 2 to 3 days, consult your veterinarian.

TAKE TIME OBSERVE LABEL DIRECTIONS

COMPOSITION: Each fluid ounce (2 tablespoonfuls) contains:

Kaolin ... 90 gr. (5.8 g)

Pectin ..... 4 gr. (0.268 g)

In a palatable vehicle.

Flavorings and color added.

STORAGE AND HANDLING

Store at controlled room temperature between 15º and 30ºC (59º - 86ºF).

Protect from freezing.

SHAKE WELL BEFORE USING.

Restriced Drug.

Use only as directed.

Not for human use.

Manufactured for:

Aspen Veterinary Resources, R Ltd.
Liberty, MO 64068

A316AP 12/11

Lot No. Exp. Date